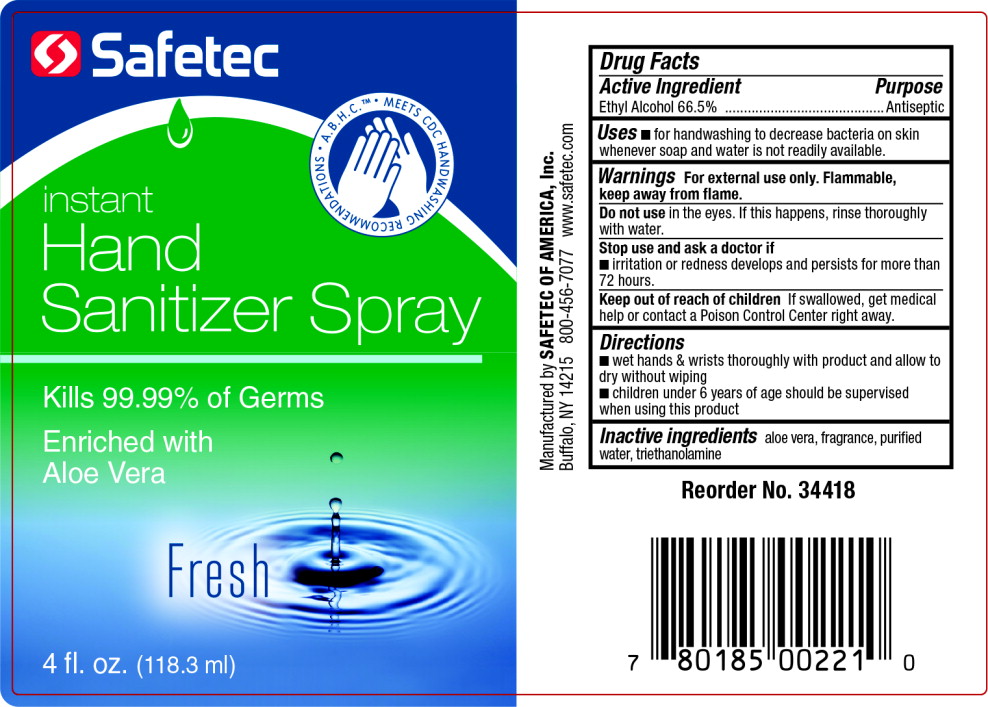 DRUG LABEL: P.A.W.S. Hand Sanitizer Bottle
NDC: 61010-3113 | Form: SPRAY
Manufacturer: Safetec 
Category: otc | Type: HUMAN OTC DRUG LABEL
Date: 20210820

ACTIVE INGREDIENTS: ALCOHOL 66.5 mL/100 mL
INACTIVE INGREDIENTS: aloe vera leaf; water; trolamine

Drug Facts

Active Ingredient

Ethyl Alcohol 66.5%

Purpose

Antiseptic

Uses

- for handwashing to decrease bacteria on skin whenever soap and water is not readily available.

Warnings

For external use only. Flammable, keep away from flame.

Do not use in the eyes. If this happens, rinse thoroughly with water.

Stop use and ask a doctor if

- irritation or redness develops and persists for more than 72 hours.

Keep out of reach of children If swallowed, get medical help or contact a Poison Control Center right away.

Directions

- wet hands & wrists thoroughly with product and allow to dry without wiping
- children under 6 years of age should be supervised when using this product

Inactive ingredients

aloe vera, fragrance, purified water, triethanolamine

Principal Display Panel - 118 mL Bottle Label

Safetec

A.B.H.C. ™ MEETS CDC HANDWASHING RECOMMENDATIONS

instant
Hand
Sanitizer Spray

Kills 99.99% of Germs

Enriched with
Aloe Vera

Fresh

4 fl. oz. (118.3 ml)